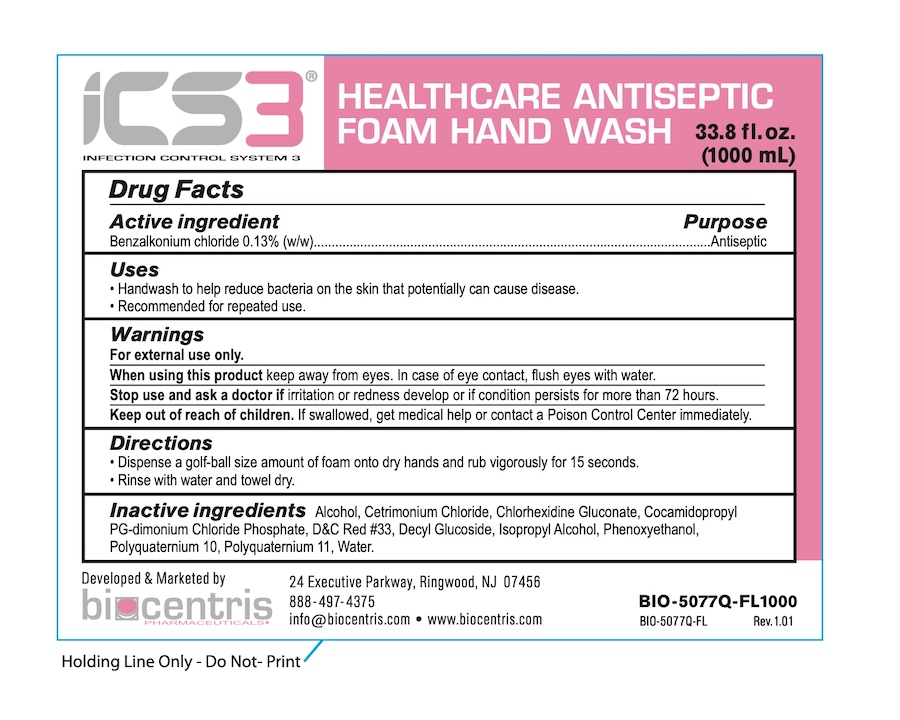 DRUG LABEL: ICS3 Pink Antiseptic Hand Wash
NDC: 81232-162 | Form: LIQUID
Manufacturer: Biocentris Pharmaceuticals, LLC
Category: otc | Type: HUMAN OTC DRUG LABEL
Date: 20210510

ACTIVE INGREDIENTS: BENZALKONIUM CHLORIDE 0.13 g/100 mL
INACTIVE INGREDIENTS: CETRIMONIUM CHLORIDE; CHLORHEXIDINE GLUCONATE; COCAMIDOPROPYL PG-DIMONIUM CHLORIDE PHOSPHATE; D&C RED NO. 33; DECYL GLUCOSIDE; ALCOHOL; PHENOXYETHANOL; POLYQUATERNIUM-10 (30000 MPA.S AT 2%); POLYQUATERNIUM-11 (1000000 MW); WATER; ISOPROPYL ALCOHOL

ICS3Pink - Antiseptic Hand Wash

Drug Facts

Active ingredient

Benzalkonium chloride 0.13% (w/w)

Purpose

Antiseptic

Uses

- Hand wash to help reduce bacteria on the skin that potentially can cause disease.
- Recommended for repeated use.

Warnings

For external use only.

When using this product keep away from eyes. In case of eye contact, flush eyes with water.

Stop use and ask a doctor if irritation or redness develop or if condition persists for more than 72 hours.

Keep out of reach of children. If swallowed, get medical help or contact a Poison Control Center immediately.

Directions

- Dispense a golf ball size amount of foam onto dry hands and rub vigorously for 15 seconds.
- Rinse with water and towel dry.

Inactive ingredients

Alcohol, Cetrimonium Chloride, Chlorhexidine Gluconate, Cocamidopropyl PG-dimonium Chloride Phosphate, D&C Red #33, Decyl Glucoside, Phenoxyethanol, Polyquaternium 10, Polyquarternium 11, Water.

Developed and Marketed by

biocentris PHARMACEUTICALS

24 Executive Parkway, Ringwood, NJ 07456

888-497-7375

info@biocentris.com • www.biocentris.com

PACKAGE LABEL

iCS3®

INFECTION CONTROL SYSTEM 3

HEALTHCARE ANTISEPTIC FOAM HAND WASH

33.8 fl. oz. (1000 mL)